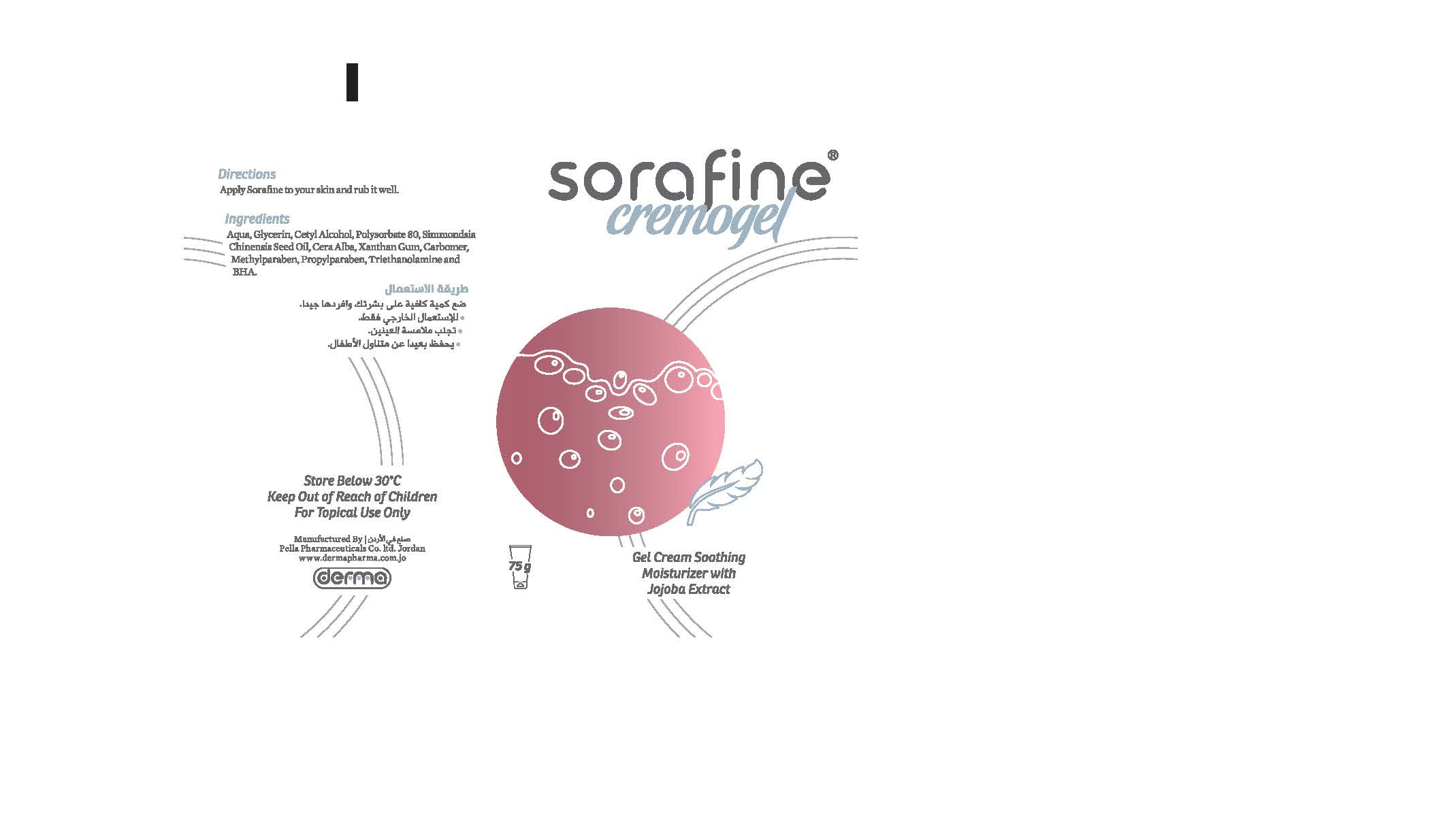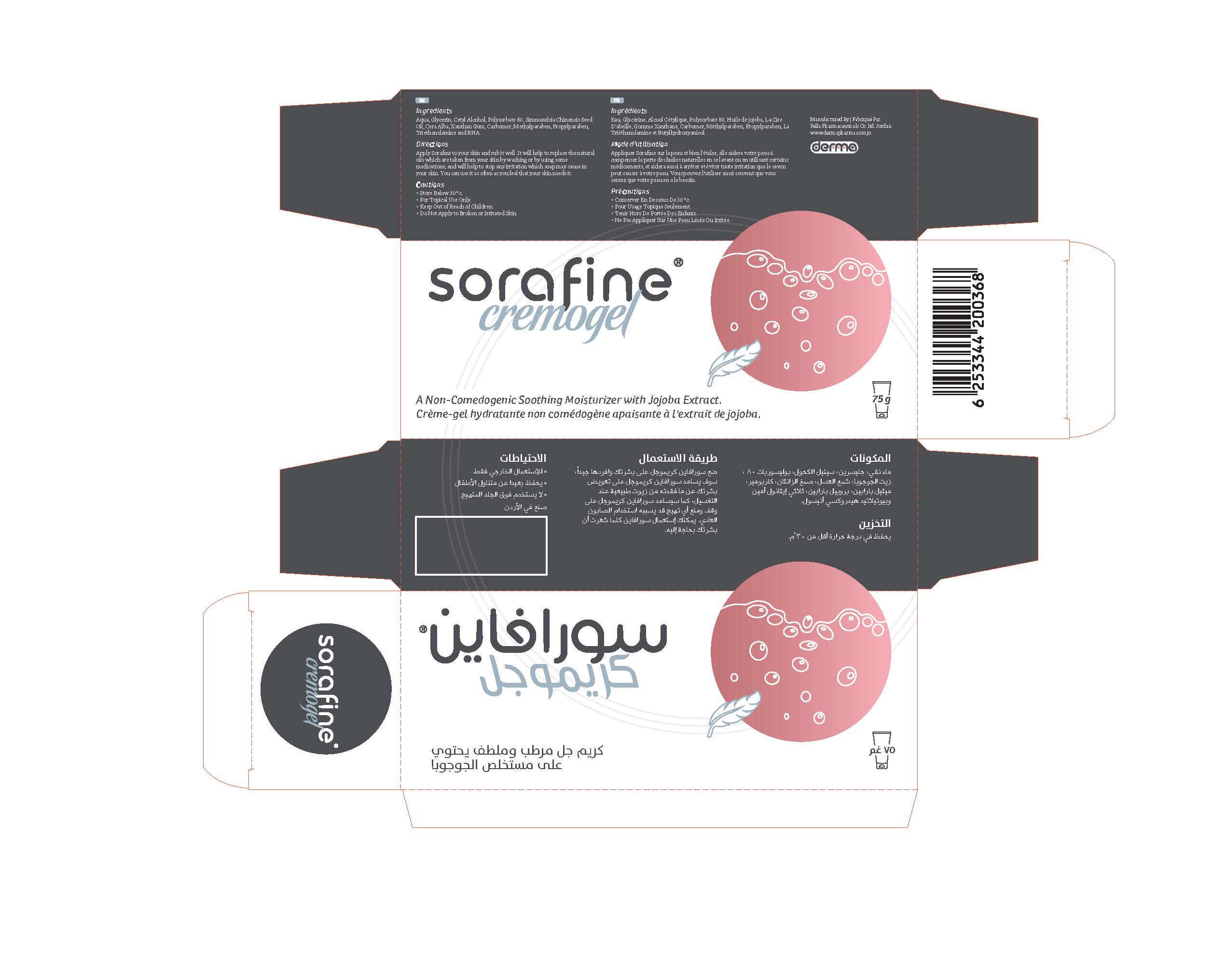 DRUG LABEL: Sorafine Cremogel
NDC: 82160-368 | Form: CREAM
Manufacturer: Pella Pharmaceuticals Co. Ltd
Category: otc | Type: HUMAN OTC DRUG LABEL
Date: 20211202

ACTIVE INGREDIENTS: JOJOBA OIL 15 mg/75 g
INACTIVE INGREDIENTS: CARBOMER 940; GLYCERIN; CETYL ALCOHOL; WATER; POLYSORBATE 80; XANTHAN GUM; PROPYLPARABEN; TROLAMINE; BUTYLATED HYDROXYANISOLE; METHYLPARABEN; WHITE WAX

Sorafine

Forms and Presentation

Cream-Gel: Tube of 75 g.

Active Ingredient

Simmondsia Chinensis (Jojoba) Seed Oil

Inactive Ingredients

Aqua, Glycerin, Cetyl Alcohol, Polysorbate 80, Cera Alba, Xanthan Gum, Carbomer, Methylparaben, Propylparaben, Triethanolamine and BHA.

Purpose

Moisturizer

Properties

Sorafine® Cremogel is a hydrating and nourishing Cream-Gel for oily and acne prone skin.
Soothing jojoba extract.

Indications

Serafine® Cremogel is used as a moisturizing and nourishing Gel - Cream for oily and acne prone skin, it is recommended for dry and sensitive skin, eczema, flaky skin, and similar skin problems.
Serafine® Cremogel prevents skin dryness and reduces roughness, relieves itching, gives a feeling of comfort and softness.
Serafine® Cremogel is distinguished by its non-fat composition, and contains jojoba oil which is suitable for oily skin, because of the similarity between its composition and the natural oils of the skin; which gives you a wonderful feeling of softness.

Precautions

Keep out of reach of children

Warnings

- For external use only
- Do not apply to broken or irritated skin.

Contraindications

Hypersensitivity to any of the components.

Side effects

Sorafine® Cremogel has no known side effects, it is used safely.

Dosage and administration

Apply Sorafine® and spread it well, it will help the skin to offset the loss of natural oils by washing or using certain medications, and also helps to stop and prevent irritation that soap can cause to the skin.
Can be used as often as needed.

Storage conditions

Store at a temperature below 30 ° C.